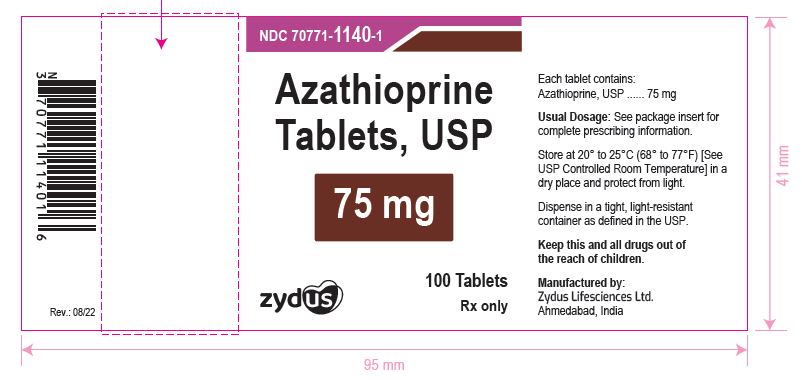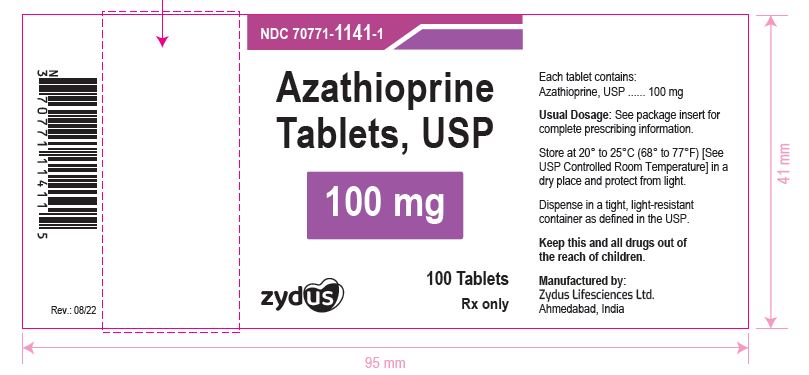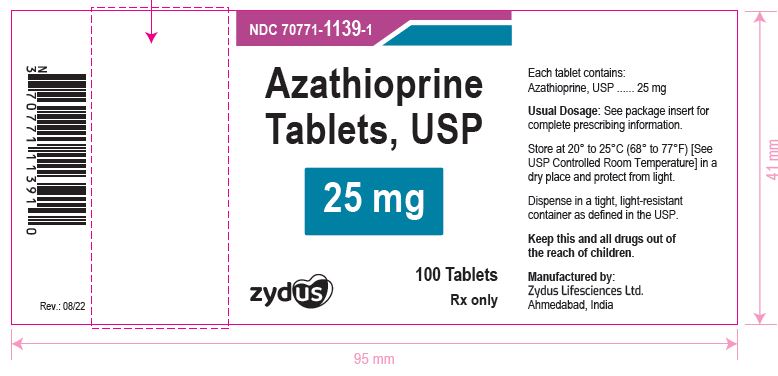 DRUG LABEL: Azathioprine
NDC: 70771-1139 | Form: TABLET
Manufacturer: Zydus Lifesciences Limited
Category: prescription | Type: HUMAN PRESCRIPTION DRUG LABEL
Date: 20241125

ACTIVE INGREDIENTS: AZATHIOPRINE 25 mg/1 1
INACTIVE INGREDIENTS: CROSCARMELLOSE SODIUM; LACTOSE MONOHYDRATE; MAGNESIUM STEARATE; POVIDONE; STARCH, CORN

Azathioprine Tablets, USP

PACKAGE LABEL.PRINCIPAL DISPLAY PANEL

NDC 70771-1140-1 in bottle of 100 tablets

Azathioprine Tablets USP, 75 mg

100 tablets

Rx only

75 mg label

PACKAGE LABEL

NDC 70771-1141-1 in bottle of 100 tablets

Azathioprine Tablets USP, 100 mg

100 tablets

Rx only

100 mg label

PACKAGE LABEL

NDC 70771-1139-1 in bottle of 100 tablets

Azathioprine Tablets USP, 25 mg

100 tablets

Rx only

25 mg label